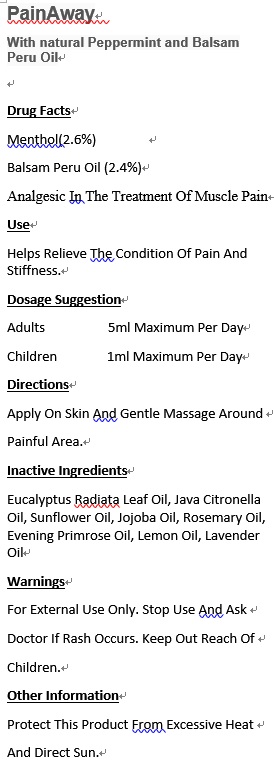 DRUG LABEL: PainAway
NDC: 70470-1118 | Form: OIL
Manufacturer: PHYTOPIA CO., LTD.
Category: otc | Type: HUMAN OTC DRUG LABEL
Date: 20191231

ACTIVE INGREDIENTS: MENTHOL 1.3 mg/50 mg; BALSAM PERU OIL 1.2 mg/50 mg
INACTIVE INGREDIENTS: LEMON OIL; EVENING PRIMROSE OIL; LAVENDER OIL; JAVA CITRONELLA OIL; SUNFLOWER OIL; JOJOBA OIL; ROSEMARY OIL; EUCALYPTUS RADIATA LEAF OIL; GAULTHERIA PROCUMBENS LEAF

Drug Facts

menthol(2.6%)

Balsam Peru Oil (2.4%)

Analgesic in the treatment of muscle pain

Use

Helps relieve the condition of pain and stiffness.

Dosage Suggestion

Adults 5ml maximum per day

Children 1ml maximum per day

Directions

Apply on skin and gentle massage around painful area.

Inactive Ingredients

EUCALYPTUS RADIATA LEAF OIL, JAVA CITRONELLA OIL, SUNFLOWER OIL, JOJOBA OIL, ROSEMARY OIL, EVENING PRIMROSE OIL, LEMON OIL, LAVENDER OIL

Warnings

For external use only. Stop use and ask doctor if rash occurs. Keep out reach of children.

Other Information

Protect this product from excessive heat

and direct sun.

Warnings

For external use only. Stop use and ask doctor if rash occurs. Keep out reach of children.